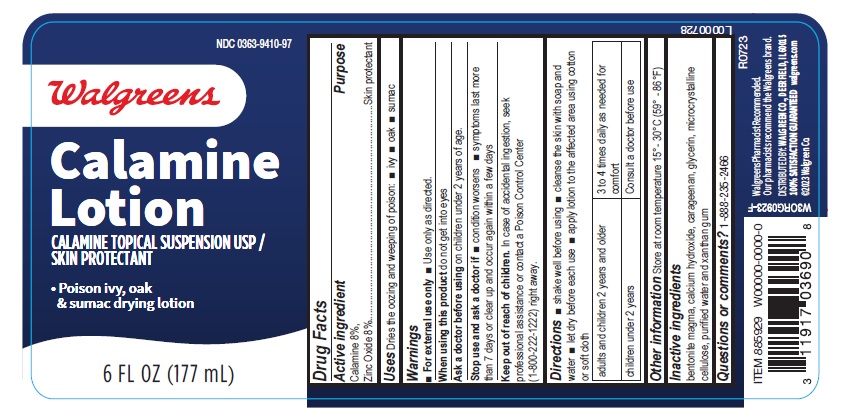 DRUG LABEL: calamine
NDC: 0363-9410 | Form: LOTION
Manufacturer: WALGREEN COMPANY
Category: otc | Type: HUMAN OTC DRUG LABEL
Date: 20241223

ACTIVE INGREDIENTS: ZINC OXIDE 160 mg/1 mL
INACTIVE INGREDIENTS: GLYCERIN; MICROCRYSTALLINE CELLULOSE; BENTONITE; CALCIUM HYDROXIDE; WATER; CARRAGEENAN; XANTHAN GUM

walgreen-calamine lotion

Active ingredient

Calamine 8%,

Zinc Oxide 8%

Purpose

Skin protectant

Uses

Dries the oozing and weeping of poison:

- ivy
- oak
- sumac

Warnings

- For external use only
- Use only as directed.

When using this product

do not get into eyes

Ask a doctor before using

on children under 2 years of age.

Stop use and ask a doctor if

- condition worsens
- symptoms last more than 7 days or clear up and occur again within a few days

Keep out of reach of children.

In case of accidental ingestion, seek professional assistance or contact a Poison Control Center (1-800-222-1222) right away.

Directions

- shake well before using
- cleanse the skin with soap and water
- let dry before each use
- apply lotion to the affected area using cotton or soft cloth

adults and children 2 years and older | 3 to 4 times daily as needed for comfort
children under 2 years | Consult a doctor before use

Other information

Store at room temperature 15°- 30°C (59° - 86°F)

Inactive ingredients

bentonite magma, calcium hydroxide, carageenan, glycerin, microcrystalline cellulose, purified water and xanthan gum

Questions or comments?

1-888-235-2466

Walgreens Pharmacist Recommended.

Our pharmacists recommend the Walgreens brand.

DISTRIBUTED BY: WALGREEN CO., DEERFIELD, IL 60015
100% SATISFACTION GUARANTEED walgreens.com
©2023 Walgreen Co.

W3ORG0923-F

L0000728

R0723

Container label

NDC 0363-9410-97

Walgreens

Calamine

Lotion
CALAMINE TOPICAL SUSPENSION USP/

SKIN PROTECTANT

- Poison ivy, oak

& sumac drying lotion

6 FL OZ (177 mL)